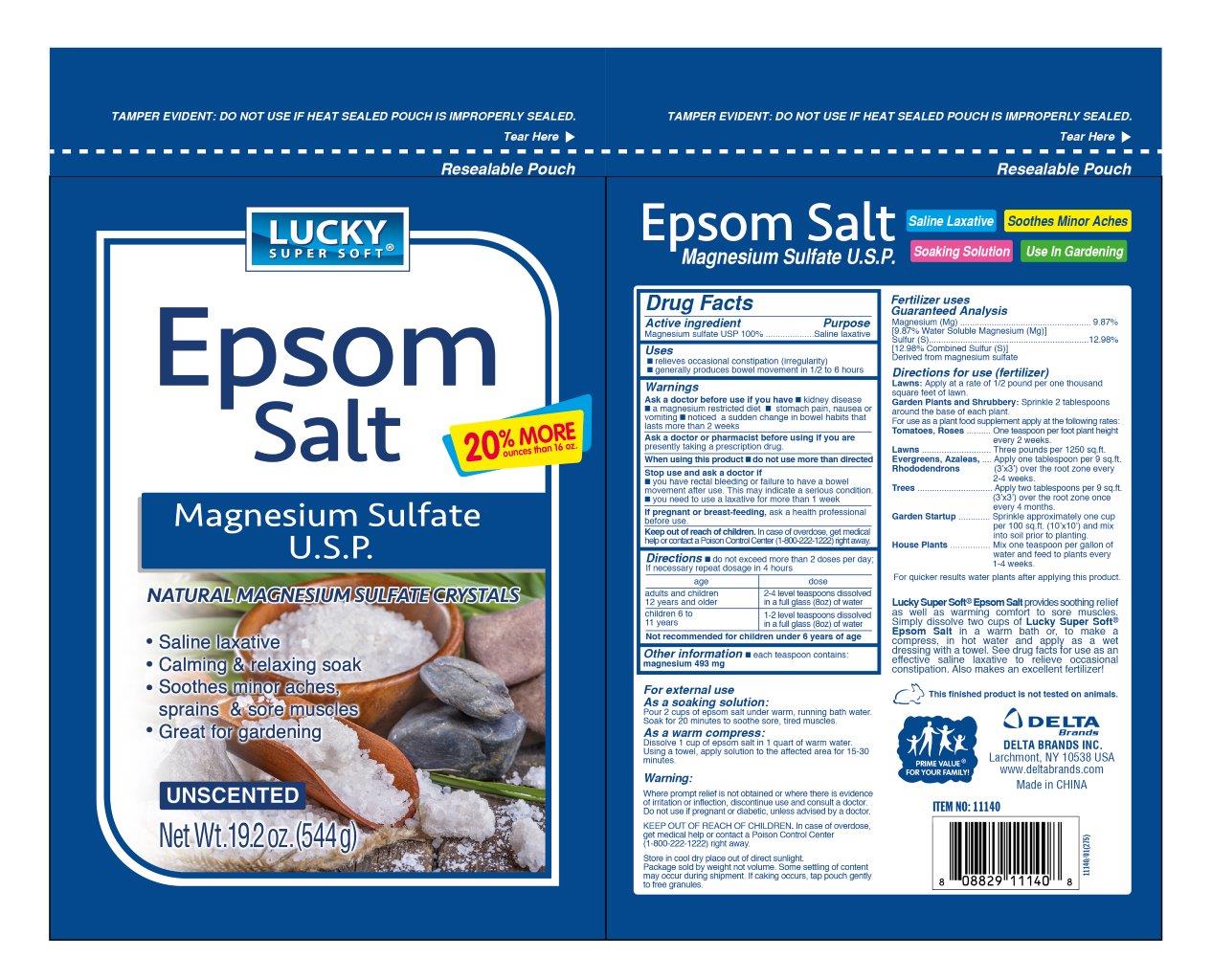 DRUG LABEL: Epsom Salt
NDC: 43221-001 | Form: GRANULE
Manufacturer: Frog Prince(China)Daily Chemicals Co., Ltd.
Category: otc | Type: HUMAN OTC DRUG LABEL
Date: 20200425

ACTIVE INGREDIENTS: MAGNESIUM SULFATE, UNSPECIFIED FORM 100 g/100 g
INACTIVE INGREDIENTS: MAGNESIUM

EPSOM SALTS

Active Ingredient

Magnesium sulfate USP 100%

Purpose

Saline laxative

Uses

■ relieves occasional constipation (irregularity)

■ generally produces bowel movement in 1/2 to 6 hours

Ask a doctor before use if you have

■ kidney disease ■ a magnesium restricted diet ■ stomach pain, nausea or vomiting ■ noticed a sudden change in bowel habits that lasts more than 2 weeks

Ask a doctor or pharmacist before using if you are

presently taking a prescription drug

When using this product

■ do not use more than directed

Stop use and ask a doctor if

■ you have rectal bleeding or failure to have a bowel movement after use. This may indicate a serious condition.

■ you need to use a laxative for more than 1 week.

If pregnant or breast-feeding

ask a health professional before use

Keep out of reach of children

In case of overdose, get medical help or contact a Poison Control Center (1-800-222-1222) right away

Directions

■do not exceed more than 2 doses per day; if necessary repeat dosage in 4 hours

age dose

adults and children 2-4 level teaspoons dissolved

12 years and older in a full glass (8oz) of water

children 6 to 1-2 level teaspoons dissolved

11 years in a full glass (8oz) of water

Not recommended for children under 6 years of age

Inactive ingredients

NONE

Other information

■ each teaspoon contains magnesium 493 mg